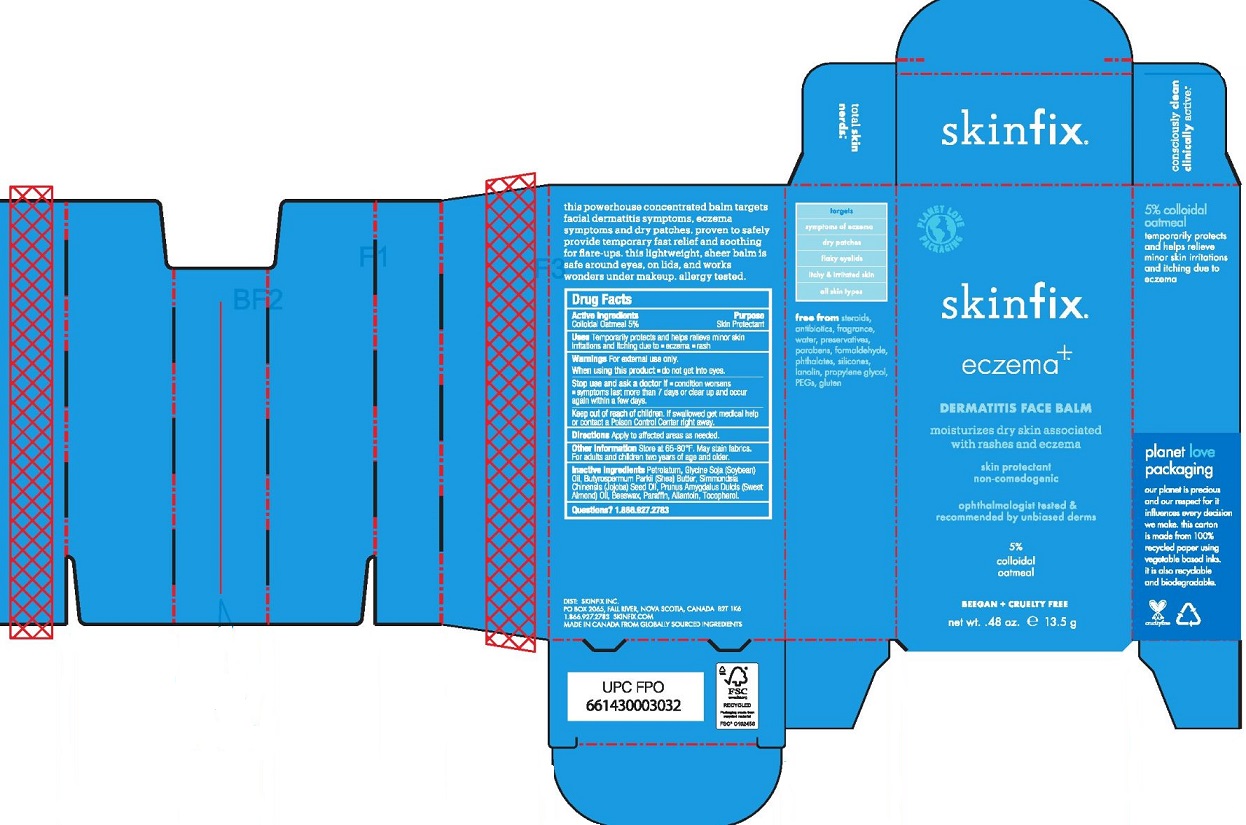 DRUG LABEL: DERMATITIS FACE BALM
NDC: 61328-121 | Form: OINTMENT
Manufacturer: Skinfix, Inc.
Category: otc | Type: HUMAN OTC DRUG LABEL
Date: 20241226

ACTIVE INGREDIENTS: OATMEAL 5 g/100 g
INACTIVE INGREDIENTS: ALLANTOIN; YELLOW WAX; SHEA BUTTER; SOYBEAN OIL; PARAFFIN; PETROLATUM; ALMOND OIL; JOJOBA OIL; TOCOPHEROL

SKINFIX - DERMATITIS FACE BALM

Active Ingredients

Colloidal Oatmeal 5%

Purpose

Skin protectant

Uses

Temporarily protects and helps relieve minor skin irritations and itching due to eczema, rash and dermatitis.

Warnings

For external use only.

Stop use and ask a doctor if

- condition worsens
- symptoms last more than 7 days or clear up and occur again within a few days.

Keep out of reach of children. If swallowed get medical help or contact a Poison Control Center right away.

Directions

Apply to affected areas as needed.

OTHER INFORMATION

STORE AT 65-75°F. MAY STAIN FABRICS. FOR ADULTS AND CHILDREN TWO YEARS OF AGE AND OLDER.

Inactive Ingredients

Petrolatum, Glycine Soja (Soybean) Oil, Butyrospermum Parkii (Shea) Butter, Simmondsia Chinensis (Jojoba) Seed Oil, Prunus Amygdalus Dulcis (Sweet Almond) Oil, Beeswax, Paraffin, Allantoin, Tocopherol.